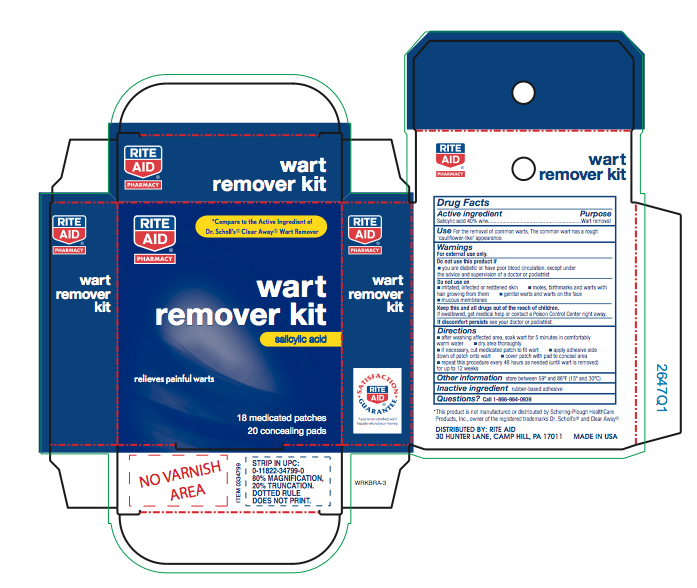 DRUG LABEL: Salicylic acid
NDC: 11822-0134 | Form: PLASTER
Manufacturer: Rite Aid Corporation
Category: otc | Type: HUMAN OTC DRUG LABEL
Date: 20250621

ACTIVE INGREDIENTS: SALICYLIC ACID 0.4 g/18 1
INACTIVE INGREDIENTS: HIGH DENSITY POLYETHYLENE

Rite Aid Wart Remover

Active ingredient

Salicylic acid 40%w/w

Purpose

Wart removal

Use

For the removal of common warts. The common wart has a rough 'cauliflower-like' appearance..

Warnings

For external use only.

Do not use this product if

you are a diabetic or have poor blood circulation, except under the advice and supervision of a doctor or podiatrist

Do not use on

- irritated, infected or reddened skin
- moles, birthmarks and warts with hair growing from them on
- genital warts and warts on the face
- mucous membranes

Keep out of reach of children.

If swallowed, get medical help or contact a Poison Control Center right away.

If discomfort persists

see your doctor or podiatrist.

Directions

- after washing affected area, soak wart for 5 minutes in comfortably warm water
- dry area thoroughly
- if necessary cut medicated patch to fit wart
- apply adhesive side down of patch onto wart
- cover patch with pad to conceal area
- repeat this procedure every 48 hours as needed (until wart is removed) for up to 12 weeks

Other information

store between 59° and 86°F (15°C and 30°C)

Inactive ingredients

acrylic adhesive, polyethylene foam

Questions?

Call 1-866-964-0939

Principal Display Panel

Rite Aid

PHARMACY

wart

remover kit

salicylic acid

relieves painful warts

18 medicated patches

20 concealing pads